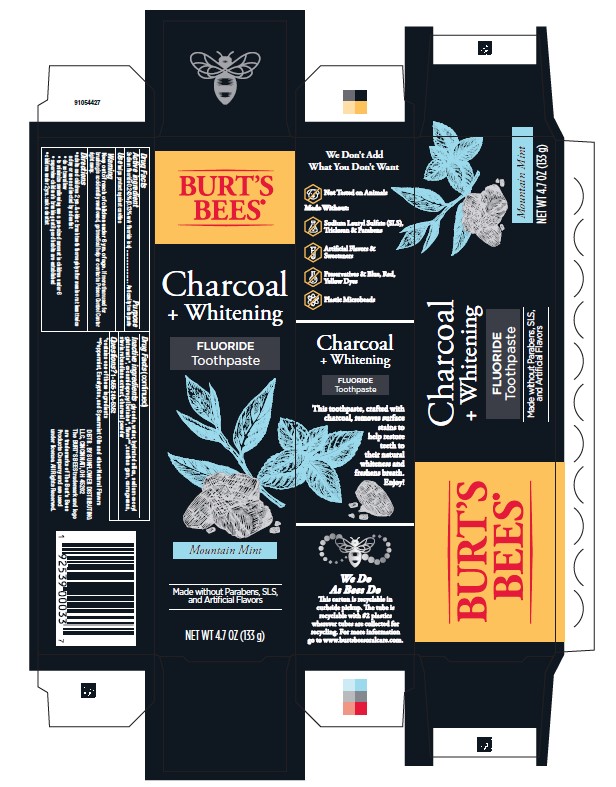 DRUG LABEL: Burts Bees
NDC: 37000-965 | Form: PASTE, DENTIFRICE
Manufacturer: Procter & Gamble Manufacturing Company
Category: otc | Type: HUMAN OTC DRUG LABEL
Date: 20260202

ACTIVE INGREDIENTS: SODIUM FLUORIDE 1.3 mg/1 g
INACTIVE INGREDIENTS: ACTIVATED CHARCOAL; CARRAGEENAN; XANTHAN GUM; WATER; HYDRATED SILICA; GLYCERIN; STEVIA REBAUDIANA WHOLE; SODIUM COCOYL GLUTAMATE; COCAMIDOPROPYL BETAINE

Burt's Bees Charcoal + Whitening

Drug Facts

Active ingredient

Sodium fluoride 0.243% (0.13% w/v fluoride ion)

Purpose

Anticavity toothpaste

Use

helps protect against cavities

Warnings

Keep out of reach of children under 6 yrs of age. If more than used for brushing is accidentally swallowed, get medical help or contact a Poison Control Center right away.

Directions

- adults and children 2 yrs. & older: brush teeth thoroughly after meals or at least twice a day or use as directed by a dentist
- do not swallow
- to minimize swallowing use a pea-sized amount in children under 6
- supervise children’s brushing until good habits are established
- children under 2 yrs.: ask a dentist

Inactive ingredients

glycerin, water, hydrated silica, sodium cocoyl glutamate*, cocamidopropyl betaine*, flavor**, xanthan gum, carrageenan, stevia rebaudiana extract, charcoal powder

Questions?

1-855-248-5352

*contains one of these ingredients

**Peppermint, Eucalyptus, and Spearmint Oils and other Natural Flavor

DISTR. BY SUNFLOWER DISTRIBUTING
LLC, CINCINNATI, OH 45202

PRINCIPAL DISPLAY PANEL - 133 g tube in carton

BURT'S

BEES®

Charcoal

+Whitening

FLUORIDE

Toothpaste

Mountain Mint

Made without Parabens, SLS, and Artificial Flavors

NET WT 4.7 OZ (133 g)